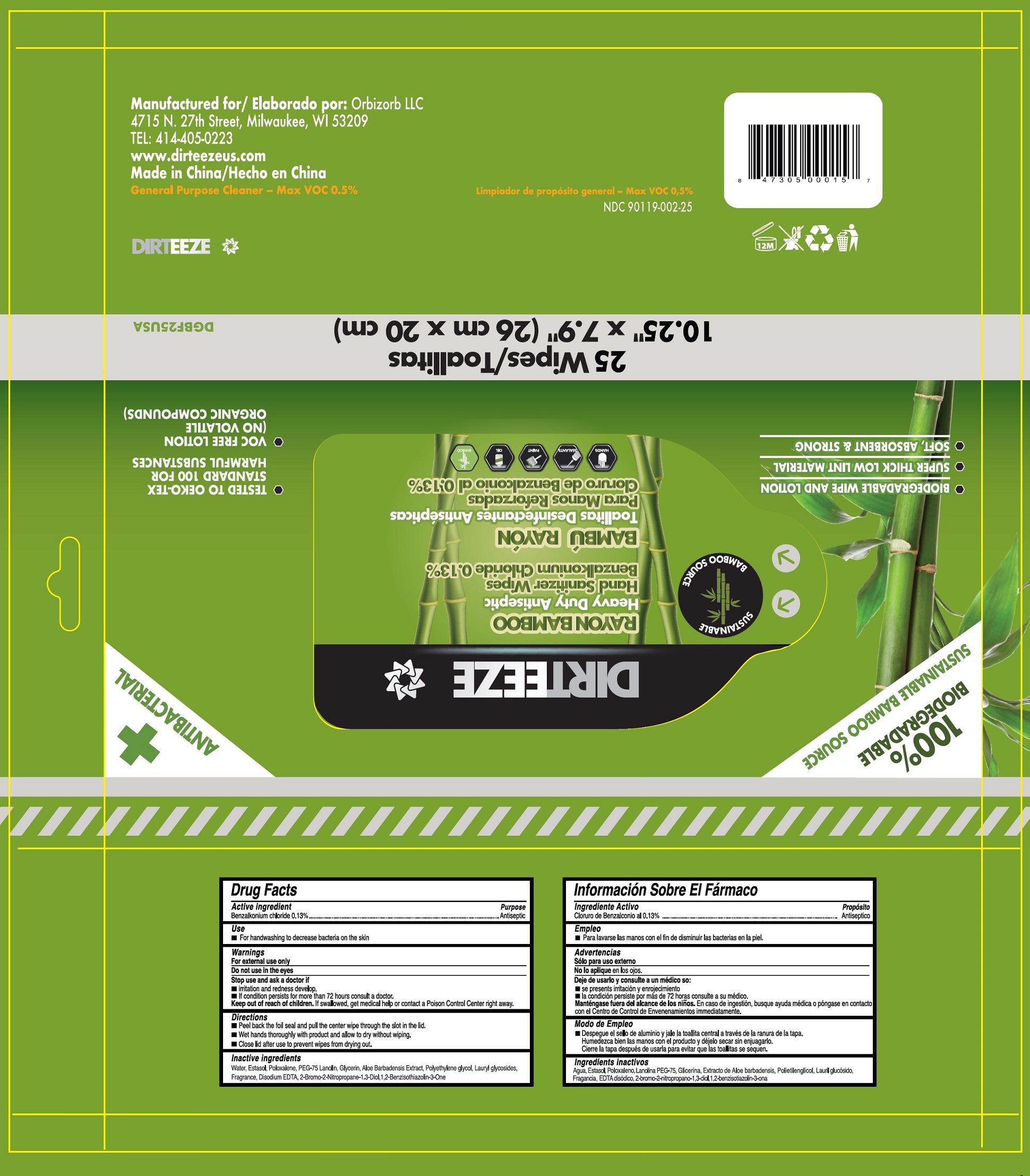 DRUG LABEL: Rayon Bamboo Heavy Duty Antiseptic Hand Sanitizer Wipes
NDC: 90119-002 | Form: CLOTH
Manufacturer: Orbizorb LLC
Category: otc | Type: HUMAN OTC DRUG LABEL
Date: 20231026

ACTIVE INGREDIENTS: BENZALKONIUM CHLORIDE 1.3 mg/1 mL
INACTIVE INGREDIENTS: BENZISOTHIAZOLINONE; WATER; POLOXALENE; PEG-75 LANOLIN; GLYCERIN; ALOE VERA LEAF; POLYETHYLENE GLYCOL, UNSPECIFIED; LAURYL GLUCOSIDE; EDETATE DISODIUM ANHYDROUS; BRONOPOL

Rayon Bamboo Heavy Duty Antiseptic Hand Sanitizer Wipes

Active ingredient

Benzalkonium Chloride 0.13%

Purpose

Antiseptic

Use

For handwashing to decrease bacteria on the skin.

Warnings

For external use only

Do not use

in the eyes

Stop use and ask a doctor if

- irritation and redness develop.
- if condition persists for more than 72 hours consult a doctor.

Keep out of reach of children.

If swallowed, get medical help or contact a Poison Control Center right away.

Directions

- Peel back the foil seal and pull the center wipe through the slot in the lid.
- Wet hands thoroughly with product and allow to dry without wiping.
- Close lid after use to prevent wipes from drying out.

Inactive ingredients

Water, Estol, Poloxalene, PEG-75 Lanolin, Glycerin, Aloe Barbadensis Extract, Polyethylene glycol, Lauryl glycoide, Fragrance, Disodium EDTA, -Bromo-2-Nitropropane-1,3-Diol, 1,2-Benzisothiazolin-3-One